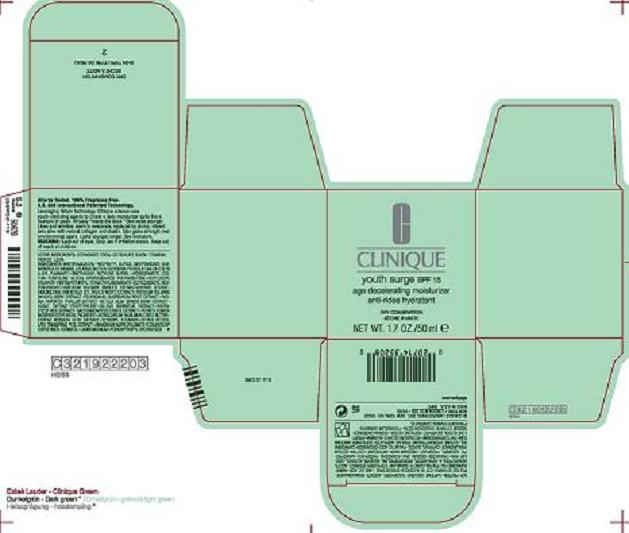 DRUG LABEL: YOUTH SURGE  
NDC: 49527-730 | Form: CREAM
Manufacturer: CLINIQUE LABORATORIES INC
Category: otc | Type: HUMAN OTC DRUG LABEL
Date: 20100402

ACTIVE INGREDIENTS: OCTINOXATE  7.50 mL/100 mL; OCTISALATE 3.5 mL/100 mL; TITANIUM DIOXIDE 1.2 mL/100 mL

ACTIVE INGREDIENT

ACTIVE INGREDIENTS: OCTINOXATE 7.5%, OCTISALATE 3.5%, TITANIUM DIOXIDE, 1.2%

WARNINGS

WARNING: KEEP OUT OF EYES. STOP USE IF IRRITATION OCCURS. KEEP OUT OF REACH OF CHILDREN.

PACKAGE LABEL

PRINCIPLE DISPLAY PANEL 1.7 OZ CARTON

CLINIQUE

YOUTH SURGE SPF 15
AGE DECELERATING MOISTURIZER
DRY COMBINATION

NET WT. 1.7 OZ/ 50 ML

CLINIQUE LABORATORIES DISTR.

NEW YORK, NY 10022

6NFC

CLINIQUE.COM